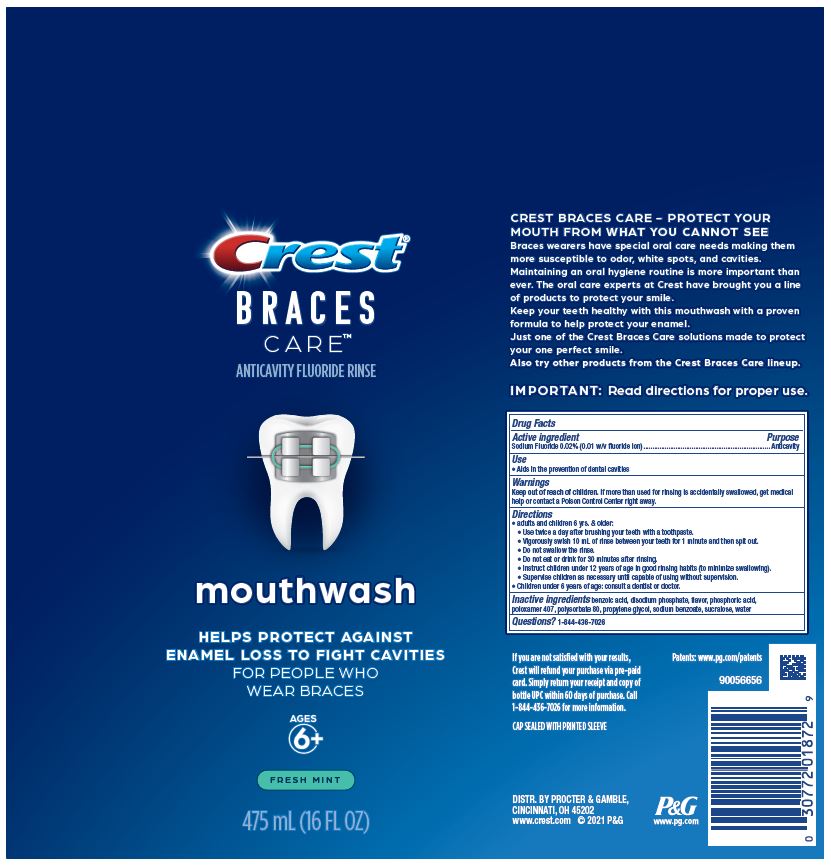 DRUG LABEL: Crest Braces Care
NDC: 69423-881 | Form: RINSE
Manufacturer: The Procter & Gamble Manufacturing Company
Category: otc | Type: HUMAN OTC DRUG LABEL
Date: 20260203

ACTIVE INGREDIENTS: SODIUM FLUORIDE 0.1 mg/1 mL
INACTIVE INGREDIENTS: WATER; BENZOIC ACID; PHOSPHORIC ACID; SODIUM BENZOATE; POLYSORBATE 80; POLOXAMER 407; SUCRALOSE; SODIUM PHOSPHATE, DIBASIC, ANHYDROUS; PROPYLENE GLYCOL

Crest Braces Care Rinse

Drug Facts

Active ingredient

Sodium Fluoride 0.02% (0.01% w/v fluoride ion)

Purpose

Anticavity

Use

Aids in the prevention of dental cavities

Warning

Keep out of reach of children. If more than used for rinsing is accidentally swallowed, get medical help or contact a Poison Control Center right away.

Directions

- Adults and children 6 years & older:
  - Use twice a day after brushing your teeth with a toothpaste.
  - Vigorously swish 10 mL of rinse between your teeth for 1 minute and then spit out.
  - Do not swallow the rinse.
  - Do not eat or drink for 30 minutes after rinsing.
  - Instruct children under 12 years of age in good rinsing habits (to minimize swallowing).
  - Supervise children as necessary until capable of using without supervision.
- Children under 6 years of age: consult a dentist or doctor.

Inactive ingredients

benzoic acid, disodium phosphate, flavor, phosphoric acid, poloxamer 407, polysorbate 80, propylene glycol, sodium benzoate, sucralose, water

Questions?

1-844-436-7026

DISTR. BY PROCTER & GAMBLE,

CINCINNATI, OH 45202

PRINCIPAL DISPLAY PANEL - 475 mL Bottle Label

Crest®

BRACES

CARE™

ANTICAVITY FLUORIDE RINSE

mouthwash

HELPS PROTECT AGAINST

ENAMEL LOSS TO FIGHT CAVITIES

FOR PEOPLE WHO

WEAR BRACES

AGES 6+

FRESH MINT

475 mL (16 FL OZ)